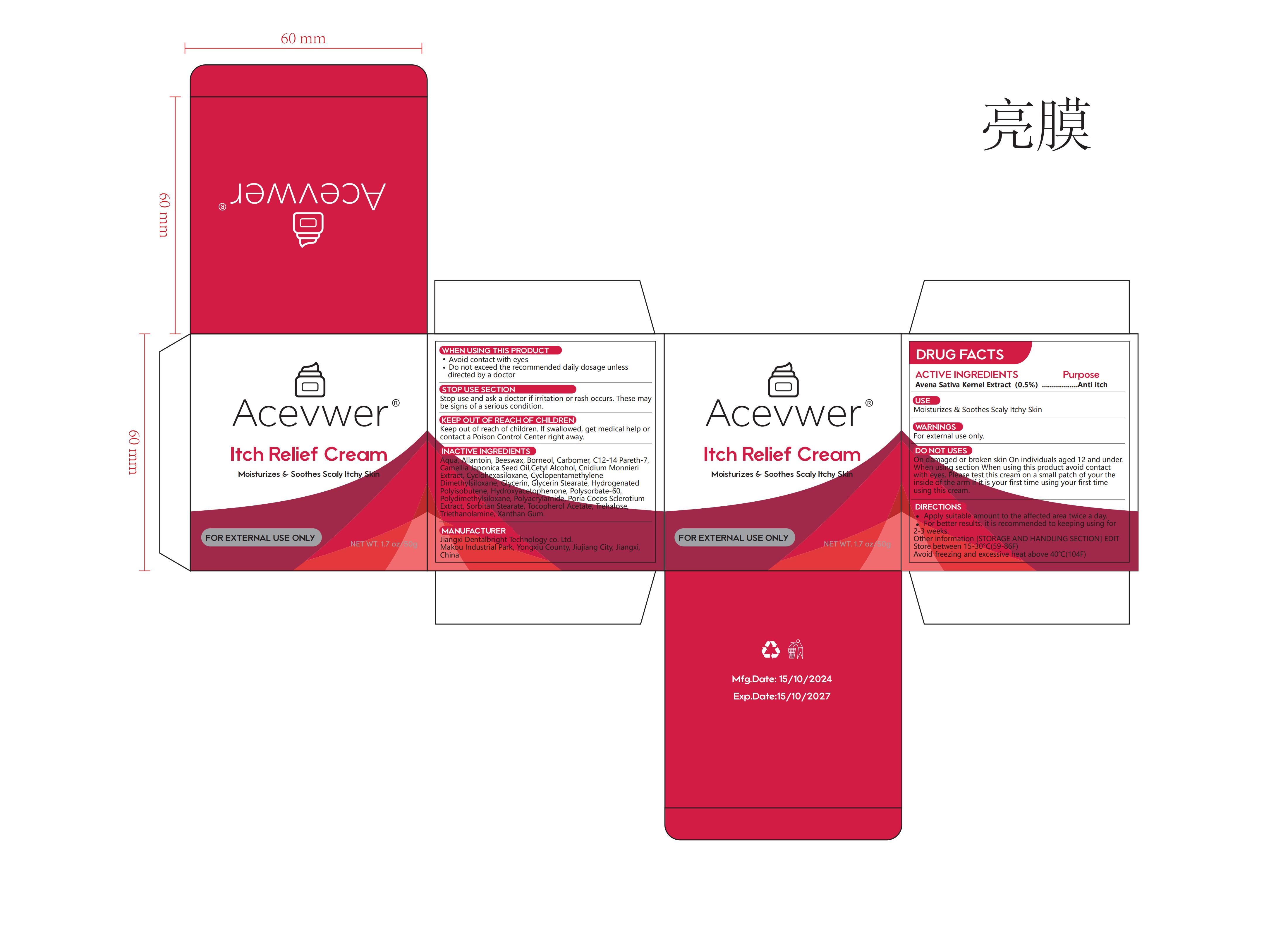 DRUG LABEL: Acevwer Itch Relief
NDC: 83778-007 | Form: CREAM
Manufacturer: Jiangxi Dentalbright Technology Co., Ltd
Category: otc | Type: HUMAN OTC DRUG LABEL
Date: 20241113

ACTIVE INGREDIENTS: AVENA SATIVA (OAT) MEAL EXTRACT 0.5 g/100 g
INACTIVE INGREDIENTS: C12-14 PARETH-7; CYCLOHEXASILOXANE; CETYL ALCOHOL; DIMETHICONE; ALLANTOIN; TROLAMINE; POLYSORBATE 60; SORBITAN STEARATE; BEESWAX; HYDROXYACETOPHENONE; CARBOMER; POLYACRYLAMIDE (CROSSLINKED; 2 MOLE PERCENT BISACRYLAMIDE); WOLFIPORIA COCOS SCLEROTIUM; BORNEOL; XANTHAN GUM; WATER; HYDROGENATED POLYISOBUTENE 8; CAMELLIA JAPONICA SEED OIL; TREHALOSE; CNIDIUM MONNIERI FRUIT OIL; GLYCERIN; CYCLOMETHICONE

83778-007

Active Ingredient

Avena Sativa Kernel Extract 0.5%

Purpose

Anti itch

Use

Moisturizes & Soothes Scaly Itchy Skin

Warnings

For external use only.

Do not use

On damaged or broken skin On individuals aged 12 and under. When using section When using this product avoid contact with eyes, Please test this cream on a small patch of your the inside of the arm if it is your first time using your first time using this cream.

When Using

.Avoid contact with eyes
.Do not exceed the recommended daily dosage unless directed by a doctor

Stop Use

Stop use and ask a doctor if irritation or rash occurs. These may be signs of a serious condition.

Ask Doctor

Ask a doctor if irritation or rash occurs. These may be signs of a serious condition.

Keep Oot Of Reach Of Children

Keep out of reach of children. lf swallowed, get medical help or contact a Poison Control Center right away.

Directions

.Apply suitable amount to the affected area twice a day.
.For better results, it is recommended to keeping using for 2-3 weeks.

Other information

[STORAGE AND HANDLING SECTION] EDIT
Store between 15-30℃(59-86F)
Avoid freezing and excessive heat above 40℃(104F)

Inactive ingredients

Aqua, Allantoin, Beeswax, Borneol, Carbomer, C12-14 Pareth-7, Camellia Japonica Seed Oil, Cetyl Alcohol, Cnidium Monnieri Extract, Cyclohexasiloxane, Cyclopentamethylene Dimethylsiloxane, Glycerin, Glycerin Stearate, Hydrogenated Polyisobutene, Hydroxyacetophenone, Polysorbate-60, Polydimethylsiloxane, Polyacrylamide, Poria Cocos Sclerotium Extract, Sorbitan Stearate, Tocopherol Acetate, Trehalose, Triethanolamine, Xanthan Gum.

Questions

Acevwer@outlook.com